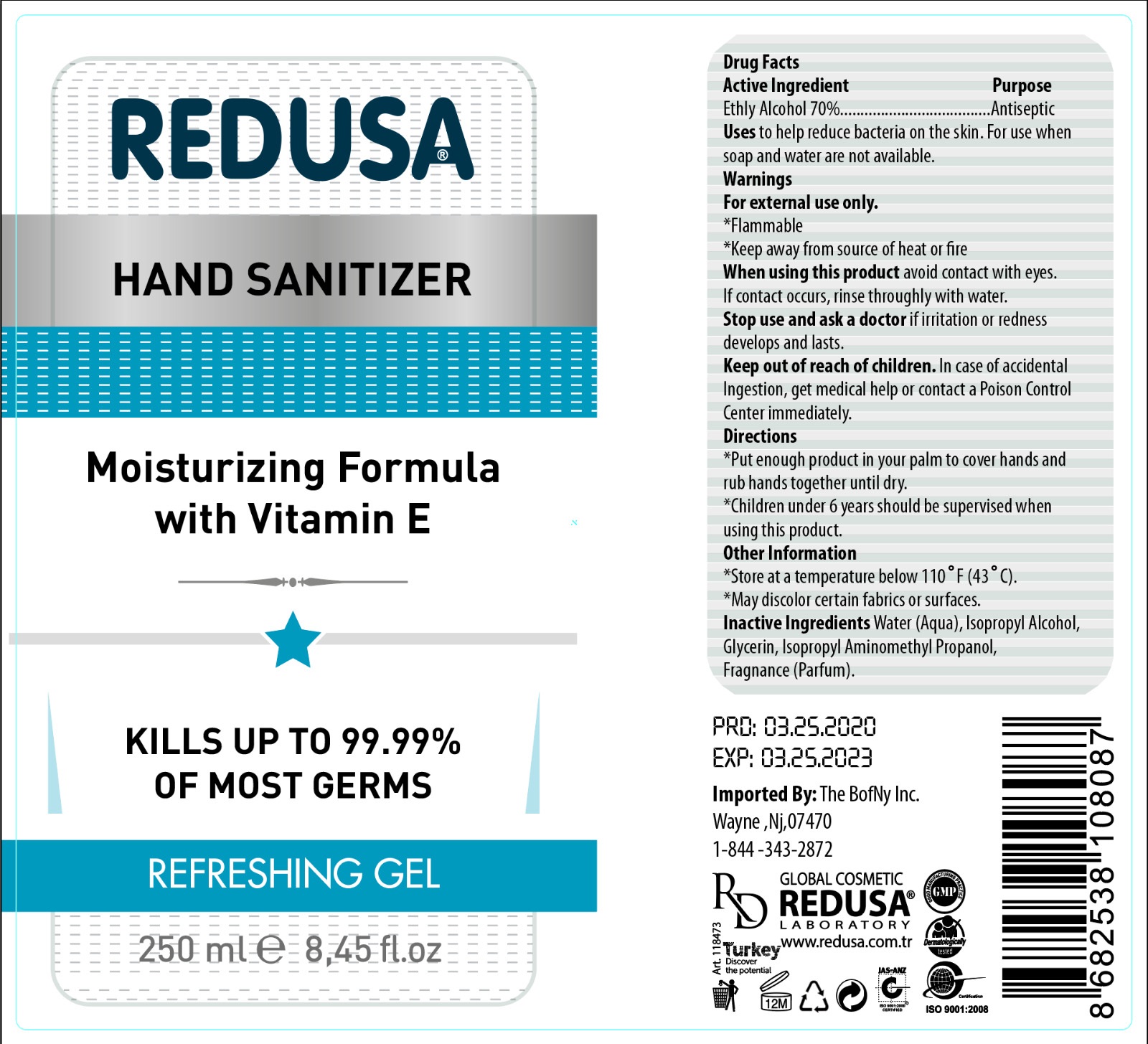 DRUG LABEL: Redusa Hand Sanitizer
NDC: 79275-000 | Form: GEL
Manufacturer: REDUSA GLOBAL KOZMETIK KISISEL BAKIM URUNLERI SANAYI VE TICARET LIMITED SIRKETI
Category: otc | Type: HUMAN OTC DRUG LABEL
Date: 20200707

ACTIVE INGREDIENTS: ALCOHOL 0.7 mL/1 mL
INACTIVE INGREDIENTS: WATER; ISOPROPYL ALCOHOL; GLYCERIN

Redusa Hand Sanitizer

Active Ingredient

Ethyl Alcohol 70%

Purpose

Antiseptic

Uses

to help reduce bacteria on the skin. For use when soap and water are not available.

Warnings

For external use only.

*Flammable

*Keep away from source of heat of fire

When using this product

avoid contact with eyes. If contact occurs, rinse throughly with water.

Stop use and ask a doctor

if irritation or redness develops and lasts.

Keep out of reach of children.

In case of accidental Ingestion, get medical help or contact a Poison Control Center immediately.

Directions

*Put enough product in your palm to cover hands and rub hands together until dry.

*Children under 6 years should be supervised when using this product.

Other Information

*Store at a temperature below 110 °F (43° C).

*May discolor certain fabrics or surfaces.

Inactive Ingredients

Water (Aqua), Isopropyl Alcohol, Glycerin, Isopropyl Aminomethyl Propanol, Fragrance (Parfum).